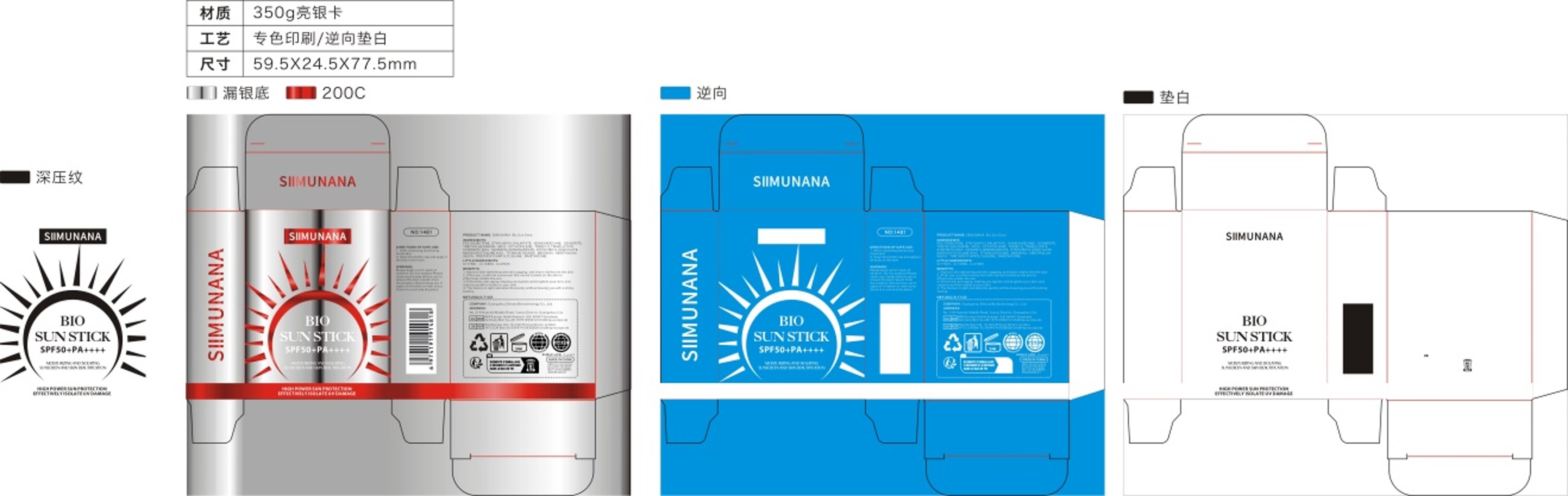 DRUG LABEL: SIIMUNANA Bio Sun Stick
NDC: 84565-001 | Form: CREAM, AUGMENTED
Manufacturer: Guangzhou Simunana Biotechnology Co., Ltd.
Category: otc | Type: HUMAN OTC DRUG LABEL
Date: 20240722

ACTIVE INGREDIENTS: OCTISALATE 4.5 g/100 g; MENTHOL 1 g/100 g
INACTIVE INGREDIENTS: MICROCRYSTALLINE WAX; YELLOW WAX; POLYISOBUTYLENE (1000 MW); SILICON DIOXIDE; MICA; TITANIUM DIOXIDE; 2-ETHYLHEXYL ISOHEXADECANOATE; CERESIN; TRIETHOXYCAPRYLYLSILANE; D&C YELLOW NO. 10; ISONONYL ISONONANOATE; D&C RED NO. 6; TRIETHYLHEXANOIN; ISOCETANE; DIMETHICONE; OCTOCRYLENE; SYNTHETIC WAX (1200 MW); TRIDECYL TRIMELLITATE

SIIMUNANA Bio Sun Stick

ACTIVE INGREDIENT

ETHYLHEXYL SALICYLATE 4.5%
MENTHOLUM 1%

PURPOSE

MOISTURIZING AND ISOLATING
SUNSCREEN AND SKIN BEAUTIFICATION

KEEP OUT OF REACH OF CHILDREN SECTION

INDICATIONS AND USAGE

MOISTURIZING AND ISOLATING
SUNSCREEN AND SKIN BEAUTIFICATION

WARNINGS

For external use only

DOSAGE AND ADMINISTRATION

Apply evenly on the skin

STORAGE AND HANDLING

SHELE LIFE:3 years

INACTIVE INGREDIENT

POLYISOBUTENE
ETHYLHEXYL PALMITATE
ISOHEXADECANE
OZOKERITE
TRIETHYLHEXANOIN
MICA
OCTOCRYLENE
TRIDECYL TRIMELLITATE
SYNTHETIC WAX
ISONONYL ISONONANOATE

MICROCRYSTALLINE WAX

TITANIUM DIOXIDE
BEESWAX

SILICA
TRIETHOXYCAPRYLYLSILANE
DIMETHICONE
CI 77891
CI 15850
CI 47005